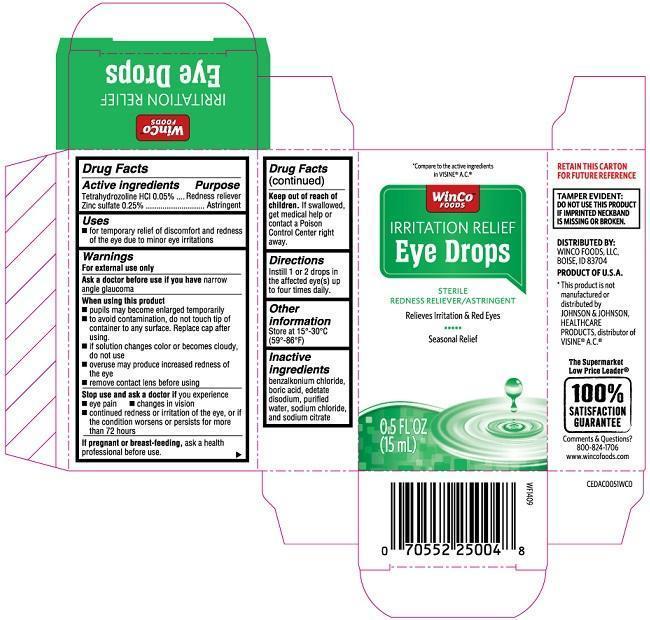 DRUG LABEL: Winco Irritation Relief Eye
NDC: 67091-283 | Form: SOLUTION/ DROPS
Manufacturer: WinCo Foods, LLC
Category: otc | Type: HUMAN OTC DRUG LABEL
Date: 20251230

ACTIVE INGREDIENTS: TETRAHYDROZOLINE HYDROCHLORIDE 50 mg/100 mL; ZINC SULFATE 250 mg/100 mL
INACTIVE INGREDIENTS: BENZALKONIUM CHLORIDE; BORIC ACID; EDETATE DISODIUM; WATER; SODIUM CHLORIDE; SODIUM CITRATE

Winco Irritation Relief (PLD)

Active ingredients

Tetrahydrozoline HCl 0.05%

Zinc sulfate 0.25%

Purpose

Tetrahydrozoline HCl...Redness Reliever

Zinc sulfate...Astringent

Uses

- for temporary relief of discomfort and redness of the eye due to minor eye irritations

Warnings

For external use only

Ask a doctor before use if you have narrow angle glaucoma

When using this product

- pupils may become enlarged temporarily
- to avoid contamination, do not touch tip of container to any surface. Replace cap after using.
- if solution changes color or becomes cloudy, do not use
- overuse may produce increased redness of the eye
- remove contact lens before using

Stop use and ask a doctor if you experience

- eye pain
- changes in vision
- continued redness or irritation of the eye, or if the condition worsens or persists for more than 72 hours

PREGNANCY

If pregnant or breast-feeding, ask a health professional before use.

Keep out of reach of children. If swallowed, get medical help or contact a Poison Control Center right away.

Directions

Instill 1 or 2 drops in the affected eye(s) up to four times daily.

Other information

Store at 15°-30°C (59°-86°F)

Inactive ingredients

benzalkonium chloride, boric acid, edetate disodium, purified water, sodium chloride, and sodium citrate